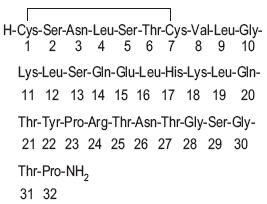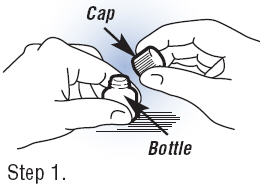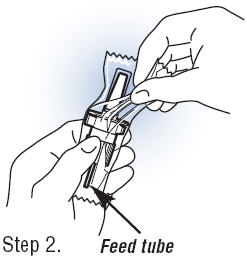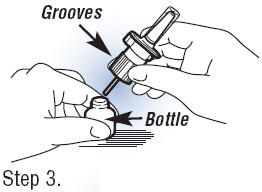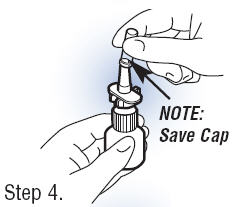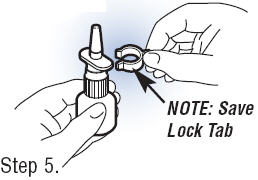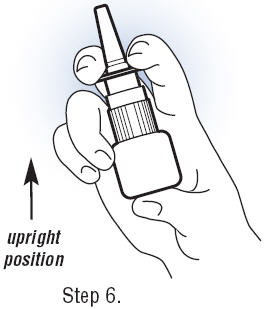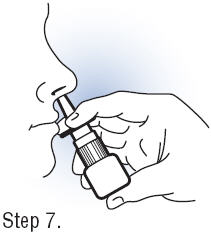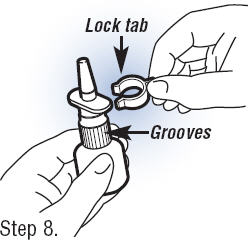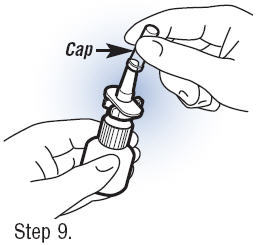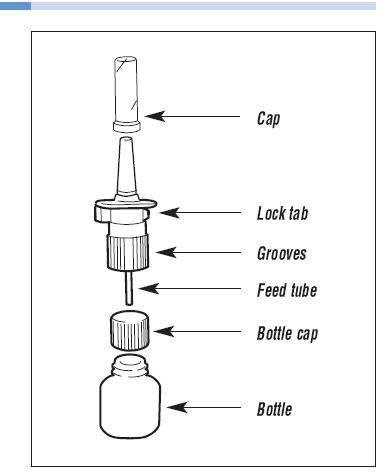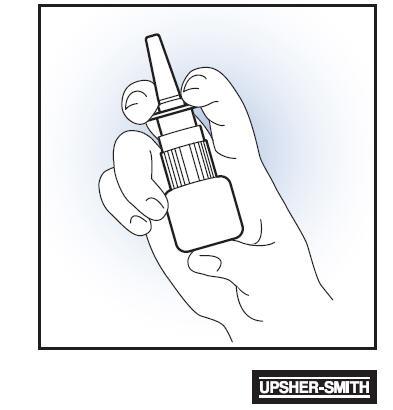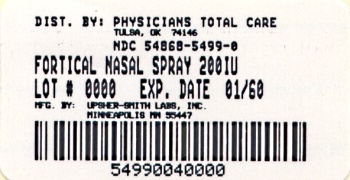 DRUG LABEL: Fortical
NDC: 54868-5499 | Form: SPRAY, METERED
Manufacturer: Physicians Total Care, Inc.
Category: prescription | Type: HUMAN PRESCRIPTION DRUG LABEL
Date: 20100115

ACTIVE INGREDIENTS: CALCITONIN SALMON 2200 [iU]/1 mL
INACTIVE INGREDIENTS: SODIUM CHLORIDE; CITRIC ACID MONOHYDRATE; PHENETHYL ALCOHOL; BENZYL ALCOHOL; POLYSORBATE 80; HYDROCHLORIC ACID; SODIUM HYDROXIDE; WATER

FORTICAL®
calcitonin-salmon
(rDNA origin)
Nasal Spray

For Intranasal Use Only

Rx only

DESCRIPTION

Calcitonin is a polypeptide hormone secreted by the parafollicular cells of the thyroid gland in mammals and by the ultimobranchial gland of birds and fish.

The active ingredient in FORTICAL® calcitonin-salmon (rDNA origin) Nasal Spray is a polypeptide of 32 amino acids manufactured by recombinant DNA technology and is identical to calcitonin-salmon produced by chemical synthesis.

This is shown by the following graphic formula:

It is provided in a 3.7 mL fill glass bottle as a solution for intranasal administration with sufficient medication for at least 30 doses. Each spray delivers 200 International Units calcitonin-salmon in a volume of 0.09 mL.

Active Ingredient: Calcitonin-salmon 2200 International Units/mL, corresponding to 200 International Units per actuation (0.09 mL).

Inactive Ingredients: Sodium Chloride USP, Citric Acid USP, Phenylethyl Alcohol USP, Benzyl Alcohol NF, Polysorbate 80 NF, Hydrochloric Acid NF or Sodium Hydroxide NF (added as necessary to adjust pH) and Purified Water USP.

CLINICAL PHARMACOLOGY

Calcitonin acts primarily on bone, but direct renal effects and actions on the gastrointestinal tract are also recognized. Calcitonin-salmon appears to have actions essentially identical to calcitonins of mammalian origin, but its potency per mg is greater and it has a longer duration of action.

The information below, describing the clinical pharmacology of calcitonin, has been derived from studies with injectable calcitonin. The mean bioavailability of calcitonin-salmon nasal spray is approximately 3% of the injectable calcitonin in normal subjects and, therefore, the conclusions concerning the CLINICAL PHARMACOLOGY of this preparation may be different.

The actions of calcitonin on bone and its role in normal human bone physiology are still not completely elucidated, although calcitonin receptors have been discovered in osteoclasts and osteoblasts.

Single injections of calcitonin cause a marked transient inhibition of the ongoing bone resorptive process. With prolonged use, there is a persistent, smaller decrease in the rate of bone resorption. Histologically, this is associated with a decreased number of osteoclasts and an apparent decrease in their resorptive activity. In vitro studies have shown that calcitonin-salmon causes inhibition of osteoclast function with loss of the ruffled osteoclast border responsible for resorption of bone. This activity resumes following removal of calcitonin-salmon from the test system. There is some evidence from in vitro studies that bone formation may be augmented by calcitonin through increased osteoblastic activity.

Animal studies indicate that endogenous calcitonin, primarily through its action on bone, participates with parathyroid hormone in the homeostatic regulation of blood calcium. Thus, high blood calcium levels cause increased secretion of calcitonin which, in turn, inhibits bone resorption. This reduces the transfer of calcium from bone to blood and tends to return blood calcium towards the normal level. The importance of this process in humans has not been determined. In normal adults, who have a relatively low rate of bone resorption, the administration of exogenous calcitonin results in only a slight decrease in serum calcium in the limits of the normal range. In normal children and in patients with Paget's disease in whom bone resorption is more rapid, decreases in serum calcium are more pronounced in response to calcitonin.

Bone biopsy and radial bone mass studies at baseline and after 26 months of daily injectable calcitonin indicate that calcitonin therapy results in the formation of normal bone.

Postmenopausal Osteoporosis

Osteoporosis is a disease characterized by low bone mass and architectural deterioration of bone tissue leading to enhanced bone fragility and a consequent increase in fracture risk as patients approach or fall below a bone mineral density associated with increased frequency of fracture. The most common type of osteoporosis occurs in postmenopausal women. Osteoporosis is a result of a disproportionate rate of bone resorption compared to bone formation, which disrupts the structural integrity of bone, rendering it more susceptible to fracture. The most common sites of these fractures are the vertebrae, hip, and distal forearm (Colles' fracture). Vertebral fractures occur with the highest frequency and are associated with back pain, spinal deformity and a loss of height.

Calcitonin, given by the intranasal route, has been shown to increase spinal bone mass in postmenopausal women with established osteoporosis but not in early postmenopausal women.

Calcium Homeostasis

In two clinical studies designed to evaluate the pharmacodynamic response to calcitonin-salmon nasal spray, administration of 100-1600 International Units to healthy volunteers resulted in rapid and sustained small decreases (but still within the normal range) in both total serum calcium and serum ionized calcium. Single doses greater than 400 International Units did not produce any further biological response to the drug. The development of hypocalcemia has not been reported in studies in healthy volunteers or postmenopausal women.

Kidney

Studies with injectable calcitonin show increases in the excretion of filtered phosphate, calcium, and sodium by decreasing their tubular reabsorption. Comparable studies have not been conducted with FORTICAL® calcitonin-salmon (rDNA origin) Nasal Spray.

Gastrointestinal Tract

Some evidence from studies with injectable preparations suggests that calcitonin may have significant actions on the gastrointestinal tract. Short-term administration of injectable calcitonin results in marked transient decreases in the volume and acidity of gastric juice and in the volume and the trypsin and amylase content of pancreatic juice. Whether these effects continue to be elicited after each injection of calcitonin during chronic therapy has not been investigated. These studies have not been conducted with FORTICAL® calcitonin-salmon (rDNA origin) Nasal Spray.

Pharmacokinetics and Drug Metabolism

The pharmacokinetic properties of FORTICAL® calcitonin-salmon (rDNA origin) Nasal Spray after multiple dose administration were shown to be similar to that of a commercially available calcitonin-salmon product in healthy volunteers. The bioavailability of calcitonin-salmon nasal spray relative to intramuscular administration is between 3 and 5%. Calcitonin-salmon nasal spray is absorbed by the nasal mucosa with a mean Tmax of about 13 minutes. The terminal half-life of calcitonin-salmon has been calculated to be around 18 minutes and no evidence of accumulation was observed with multiple dosing. Plasma exposure was higher following administration of 400 IU nasal spray compared to that after 200 IU dose. As is the case with other polypeptide hormones, there is very little value in monitoring plasma levels of salmon calcitonin since these are not directly predictive of the therapeutic response. Hence, Fortical® activity should be evaluated by using clinical parameters of efficacy.

INDICATIONS AND USAGE

Postmenopausal Osteoporosis

FORTICAL® calcitonin-salmon (rDNA origin) Nasal Spray is indicated for the treatment of postmenopausal osteoporosis in women greater than 5 years postmenopause with low bone mass relative to healthy premenopausal women. Use of FORTICAL® calcitonin-salmon (rDNA origin) Nasal Spray is recommended in conjunction with an adequate calcium (at least 1000 mg elemental calcium per day) and Vitamin D (400 International Units per day) intake to retard the progressive loss of bone mass. The evidence of efficacy for calcitonin-salmon is based on increases in spinal bone mineral density (BMD) observed in clinical trials.

Two randomized, placebo-controlled trials were conducted in 325 postmenopausal women (227 treated with calcitonin-salmon nasal spray and 98 treated with placebo) with spinal, forearm or femoral BMD at least one standard deviation below the normal value for healthy premenopausal women. These studies conducted over two years demonstrated that 200 International Units daily of calcitonin-salmon nasal spray increases lumbar vertebral BMD relative to baseline and relative to placebo in osteoporotic women who were greater than 5 years postmenopause. Calcitonin-salmon nasal spray produced statistically significant increases in lumbar vertebral BMD compared to placebo as early as 6 months after initiation of therapy with persistence of this level for up to 2 years of observation.

No effects of calcitonin-salmon nasal spray on cortical bone of the forearm or hip were demonstrated. However, in one study, BMD of the hip showed a statistically significant increase compared with placebo in a region composed of predominantly trabecular bone after 1 year of treatment changing to a trend at 2 years that was no longer statistically significant.

CONTRAINDICATIONS

Clinical allergy to calcitonin-salmon.

WARNINGS

Allergic Reactions

Because calcitonin is a polypeptide, the possibility of a systemic allergic reaction exists. A few cases of serious allergic-type reactions have been reported in patients receiving calcitonin-salmon nasal spray, including cases of anaphylaxis and anaphylactic shock. With injectable calcitonin-salmon there have been a few reports of serious allergic-type reactions (e.g. bronchospasm, swelling of the tongue or throat, anaphylactic shock), including very rare reports of death attributed to anaphylaxis. The usual provisions should be made for emergency treatment if such a reaction should occur. Allergic reactions should be differentiated from generalized flushing and hypotension.

For patients with suspected sensitivity to calcitonin, skin testing should be considered prior to treatment utilizing a dilute, sterile solution of a calcitonin-salmon injectable product. Physicians may wish to refer patients who require skin testing to an allergist. A detailed skin testing protocol is available from Upsher-Smith Laboratories, Inc. by calling toll-free at 1-800-654-2299.

PRECAUTIONS

1. Drug Interactions

Formal studies designed to evaluate drug interactions with calcitonin-salmon have not been done.

Concomitant use of calcitonin and lithium may lead to a reduction in plasma lithium concentrations due to increased urinary clearance of lithium. The dose of lithium may need to be adjusted.

The effects of prior use of diphosphonates in postmenopausal osteoporosis patients have not been assessed; however, in patients with Paget's disease prior diphosphonate use appears to reduce the anti-resorptive response to calcitonin-salmon nasal spray.

2. Periodic Nasal Examinations

Periodic nasal examinations with visualization of the nasal mucosa, turbinates, septum and mucosal blood vessel status are recommended.

The development of mucosal alterations or transient nasal conditions have been reported in up to 9% of patients who received a calcitonin-salmon nasal spray and in up to 12% of patients who received placebo nasal spray in studies in postmenopausal women. The majority of patients (approximately 90%) in whom nasal abnormalities were noted also reported nasally related complaints/symptoms as adverse events. Therefore, a nasal examination should be performed prior to start of treatment with nasal calcitonin and at any time nasal complaints occur.

In all postmenopausal patients treated with a calcitonin-salmon nasal spray, the most commonly reported nasal adverse events included rhinitis (12%), epistaxis (3.5%), and sinusitis (2.3%). Smoking was shown not to have any contributory effect on the occurrence of nasal adverse events. One patient (0.3%) treated with a calcitonin-salmon nasal spray who was receiving 400 International Units daily developed a small nasal wound. In clinical trials in another disorder (Paget's disease), 2.8% of patients developed nasal ulcerations.

If severe ulceration of the nasal mucosa occurs, as indicated by ulcers greater than 1.5 mm in diameter or penetrating below the mucosa, or those associated with heavy bleeding, calcitonin-salmon nasal spray should be discontinued. Although smaller ulcers often heal without withdrawal of calcitonin-salmon nasal spray, medication should be discontinued temporarily until healing occurs.

3. Information for Patients

Careful instructions on pump assembly, priming of the pump and nasal introduction of FORTICAL® calcitonin-salmon (rDNA origin) Nasal Spray should be given to the patient. Although instructions for patients are supplied with the individual bottle, procedures for use should be demonstrated to each patient. Patients should notify their physician if they develop significant nasal irritation.

Get emergency medical help right away if you have any of the following symptoms of a serious allergic reaction:

- trouble breathing
- swelling of your face, throat or tongue
- rapid heartbeat
- chest pain
- feel faint or dizzy

Patients should be advised of the following:

- Store new, unassembled bottles in the refrigerator between 36-46°F (2-8°C).
- Protect the product from freezing.
- Keep the bottle of Fortical® Nasal Spray away from light.
- Before priming the pump and using a new bottle, allow it to reach room temperature.
- After opening a new bottle of Fortical® Nasal Spray, store bottle in use with pump attached at room temperature, 68°F to 77°F (20°C to 25°C), in an upright position. Each bottle contains enough medicine for 30 doses.
- Throw away the empty bottle of Fortical® Nasal Spray after you have used 30 doses.
- See DOSAGE AND ADMINISTRATION, Priming (Activation) of Pump for complete instructions on priming the pump and administering FORTICAL® calcitonin-salmon (rDNA origin) Nasal Spray.

4. Carcinogenicity, Mutagenicity, Impairment of Fertility

An increased incidence of non-functioning pituitary adenomas has been observed in 1-year toxicity studies in Sprague-Dawley and Fischer 344 Rats administered (subcutaneously) calcitonin-salmon at dosages of 80 International Units per kilogram per day (16-19 times the recommended human parenteral dose and about 130-160 times the human intranasal dose based on body surface area).

The findings suggest that calcitonin-salmon reduced the latency period for development of the pituitary adenomas that do not produce hormones, probably through the perturbation of physiologic processes involved in the evolution of this commonly occurring endocrine lesion in the rat. Although administration of calcitonin-salmon reduces the latency period of the development of nonfunctional proliferative lesions in rats, it did not induce the hyperplastic/neoplastic process.

Calcitonin-salmon was tested for mutagenicity using four strains of Salmonella typhimurium and two strains of Escherichia coli, with and without rat liver metabolic activation, and found to be non-mutagenic. The drug was also not mutagenic in a chromosome aberration test in Chinese Hamster ovary cells in vitro.

5. Laboratory Tests

Urine sediment abnormalities have not been reported in ambulatory volunteers treated with calcitonin-salmon nasal spray. Coarse granular casts containing renal tubular epithelial cells were reported in young adult volunteers at bed rest who were given injectable calcitonin-salmon to study the effect of immobilization on osteoporosis. There was no evidence of renal abnormality and the urine sediment became normal after calcitonin was stopped. Periodic examinations of urine sediment should be considered.

6. Pregnancy

Teratogenic Effects

Category C

Calcitonin-salmon has been shown to cause a decrease in fetal birth weights in rabbits when given by injection in doses 8-33 times the parenteral dose and 70-278 times the intranasal dose recommended for human use based on body surface area.

Since calcitonin does not cross the placental barrier, this finding may be due to metabolic effects on the pregnant animal. There are no adequate and well-controlled studies in pregnant women with calcitonin-salmon. FORTICAL® calcitonin-salmon (rDNA origin) Nasal Spray is not indicated for use in pregnancy.

7. Nursing Mothers

It is not known whether this drug is excreted in human milk. As a general rule, nursing should not be undertaken while a patient is on this drug since many drugs are excreted in human milk. Calcitonin has been shown to inhibit lactation in animals.

8. Pediatric Use

There are no data to support the use of FORTICAL® calcitonin-salmon (rDNA origin) Nasal Spray in children. Disorders of bone in children referred to as idiopathic juvenile osteoporosis have been reported rarely. The relationship of these disorders to postmenopausal osteoporosis has not been established and experience with the use of calcitonin in these disorders is limited.

9. Geriatric Use

In a large multi-centered, double-blind, randomized clinical study of calcitonin-salmon nasal spray, 279 patients were less than 65 years old, while 467 patients were 65 to 74 years old and 196 patients were 75 and over. Compared to subjects less than 65 years old, the incidence of nasal adverse events (rhinitis, irritation, erythema, and excoriation) was higher in patients over the age of 65, particularly those over the age of 75. Most events were mild in intensity. Other reported clinical experience has not identified differences in responses between the elderly and younger patients, but greater sensitivity of some older individuals cannot be ruled out.

ADVERSE REACTIONS

The incidence of adverse reactions reported in studies involving postmenopausal osteoporotic patients chronically exposed to calcitonin-salmon nasal spray (N=341) and to placebo nasal spray (N=131), and reported in greater than 3% of calcitonin-salmon nasal spray treated patients are presented in the following table. Most adverse reactions were mild to moderate in severity. Nasal adverse events were most common with 70% mild, 25% moderate, and 5% severe in nature (placebo rates were 71% mild, 27% moderate, and 2% severe).

Adverse Reactions Occurring in at Least 3% of Postmenopausal Patients Treated Chronically
Adverse Reaction | Calcitonin-Salmon Nasal Spray N=341 % of Patients | Placebo N=131 % of Patients
Rhinitis | 12.0 | 6.9
Symptom of Nose [Symptom of nose includes: nasal crusts, dryness, redness or erythema, nasal sores, irritation, itching, thick feeling, soreness, pallor, infection, stenosis, runny/blocked, small wound, bleeding wound, tenderness, uncomfortable feeling and sore across bridge of nose.] | 10.6 | 16.0
Back Pain | 5.0 | 2.3
Arthralgia | 3.8 | 5.3
Epistaxis | 3.5 | 4.6
Headache | 3.2 | 4.6

In addition, the following adverse events were reported in fewer than 3% of patients during chronic therapy with calcitonin-salmon nasal spray. Adverse events reported in 1%-3% of patients are identified with an asterisk(*). The remainder occurred in less than 1% of patients. Other than flushing, nausea, possible allergic reactions, and possible local irritative effects in the respiratory tract, a relationship to calcitonin-salmon nasal spray has not been established.

Body as a whole – General Disorders: influenza-like symptoms*, fatigue*, edema (facial, peripheral, and generalized), fever

Integumentary: erythematous rash*, skin ulceration, eczema, alopecia, pruritus, increased sweating

Musculoskeletal/Collagen: arthrosis*, myalgia*, arthritis, polymyalgia rheumatica, stiffness

Respiratory/Special Senses: sinusitis*, upper respiratory tract infection*, bronchospasm*, pharyngitis, bronchitis, pneumonia, coughing, dyspnea, taste perversion, parosmia, nasal congestion, sneezing, allergic rhinitis, nasal odor, mucosal excoriation, rhinitis ulcerative

Cardiovascular: hypertension*, angina pectoris*, tachycardia, palpitation, bundle branch block, myocardial infarction

Gastrointestinal: dyspepsia*, constipation*, abdominal pain*, nausea*, diarrhea*, vomiting, flatulence, increased appetite, gastritis, dry mouth

Liver/Metabolic: cholelithiasis, hepatitis, thirst, weight increase

Endocrine: goiter, hyperthyroidism

Urinary System: cystitis*, pyelonephritis, hematuria, renal calculus

Central and Peripheral Nervous System: dizziness*, paresthesia*, vertigo, migraine, neuralgia, agitation

Hearing/Vestibular: tinnitus, hearing loss, earache

Vision: abnormal lacrimation*, conjunctivitis*, blurred vision, vitreous floater, visual disturbance

Vascular: flushing, cerebrovascular accident, thrombophlebitis

Hematologic/Resistance Mechanisms: lymphadenopathy*, infection*, anemia

Psychiatric: depression*, insomnia, anxiety, anorexia

Immune System Disorders: hypersensitivity, anaphylaxis and anaphylactic shock

Common adverse reactions associated with the use of injectable calcitonin-salmon occurred less frequently in patients treated with calcitonin-salmon nasal spray than in those patients treated with injectable calcitonin. Nausea, with or without vomiting, which occurred in 1.8% of patients treated with the nasal spray (and 1.5% of those receiving placebo nasal spray) occurs in about 10% of patients who take injectable calcitonin-salmon. Flushing, which occurred in less than 1% of patients treated with the nasal spray, occurs in 2-5% of patients treated with injectable calcitonin-salmon. Although the administered dosages of injectable and nasal spray calcitonin-salmon are comparable (50-100 units daily of injectable versus 200 units daily of nasal spray), the nasal dosage form has a mean bioavailability of about 3% (range 0.3%-30.6%) and therefore provides less drug to the systemic circulation, possibly accounting for the decrease in frequency of adverse reactions.

The collective foreign marketing experience with calcitonin-salmon nasal spray does not show evidence of any notable difference in the incidence profile of reported adverse reactions when compared with that seen in the clinical trials.

OVERDOSAGE

No instances of overdose with calcitonin-salmon nasal spray have been reported and no serious adverse reactions have been associated with high doses. There is no known potential for drug abuse for calcitonin-salmon.

Single doses of calcitonin-salmon nasal spray up to 1600 International Units, doses up to 800 International Units per day for 3 days and chronic administration of doses up to 600 International Units per day have been studied without serious adverse effects. A 1000 International Units dose of calcitonin-salmon injectable product given subcutaneously may produce nausea and vomiting. A 32 International Units per kg per day dose of calcitonin-salmon injectable product for 1or 2 days demonstrated no additional adverse effects.

There have been no reports of hypocalcemic tetany. However, the pharmacologic actions of FORTICAL® calcitonin-salmon (rDNA origin) Nasal Spray suggest that this could occur in overdose. Therefore, provisions for parenteral administration of calcium should be available for the treatment of overdose.

DOSAGE AND ADMINISTRATION

The recommended dose of FORTICAL® calcitonin-salmon (rDNA origin) Nasal Spray in postmenopausal osteoporotic patients is 1 spray (200 International Units) per day administered intranasally, alternating nostrils daily. Each bottle, filled with 3.7 mL of solution, contains enough medication for 30 doses. Drug effect may be monitored by periodic measurements of lumbar vertebral bone mass to document stabilization of bone loss or increases in bone density. Effects of calcitonin-salmon nasal spray on biochemical markers of bone turnover have not been consistently demonstrated in studies in postmenopausal osteoporosis. Therefore, these parameters should not be solely utilized to determine clinical response to calcitonin-salmon nasal spray therapy in these patients.

Priming (Activation) of Pump

Before the first dose and administration, allow the bottle to reach room temperature. Remove the protective cap and clip from the bottle of FORTICAL® calcitonin-salmon (rDNA origin) Nasal Spray. To prime the pump, hold the bottle upright and depress the two white side arms of the pump toward the bottle at least 5 times until a full spray is produced. The pump is primed once the first full spray is emitted. To administer, the nozzle should be carefully placed into the nostril with the head in the upright position and the pump firmly depressed toward the bottle. The pump should NOT be primed before each daily use.

HOW SUPPLIED

FORTICAL® calcitonin-salmon (rDNA origin) Nasal Spray is presented as a metered dose solution in a 3.7 mL fill amber glass bottle. It is available in a dosage strength of 200 International Units per activation (0.09 mL). A screw-on pump is provided.

Following priming, the pump will deliver solution containing 200 International Units of calcitonin-salmon per activation. FORTICAL® calcitonin-salmon (rDNA origin) Nasal Spray contains 2200 International Units/mL calcitonin-salmon and is provided in individual boxes containing one glass bottle with screw cap and one screw-on pump (NDC# 54868-5499-0).

Store and Dispense

Store unopened bottle in refrigerator between 36°F to 46°F (2°C to 8 °C). Protect from freezing. After opening, store bottle in use in an upright position at 68°F to 77°F (20°C to 25 °C). Excursions permitted to 15°C to 30°C (59°F to 86°F). Throw away the empty bottle of Fortical® Nasal Spray after you have used 30 doses.

Distributed by

UPSHER-SMITH LABORATORIES, INC.
Minneapolis, MN USA 55447-4709

US Patent RE 40,182
US Patent 6,103,495
US Patent 6,210,925
US Patent 6,627,438
US Patent 6,737,250
US Patent 5,789,234

104043-01
Revised 0110

Relabeling of "ADDITIONAL" Barcode Label by:
Physicians Total Care, Inc.
Tulsa, OK 74146

Fortical®calcitonin-salmon (rDNA origin) Nasal Spray

Patient Information and Instructions for Use

Patient Information

Fortical® [fōr-tǐ-kǎl]
calcitonin-salmon (rDNA origin)
Nasal Spray

Read the Patient Information that comes with Fortical® Nasal Spray before you start using it and each time you get a refill. There may be new information. This leaflet does not take the place of talking with your doctor about your medical condition or your treatment.

What is Fortical® Nasal Spray?

Fortical® Nasal Spray is a prescription medicine used to treat osteoporosis in women, who went through menopause (postmenopausal women) at least 5 years ago.

Fortical® Nasal Spray contains calcitonin salmon, a man-made protein that is similar to a protein occurring in the human body. When you spray Fortical® Nasal Spray into your nostril, it is rapidly absorbed by the blood vessels lining your nasal passages. It then travels into your bloodstream and on to your bones where it has been shown to slow down bone loss at the spine. Slowing down bone loss, while new bone building continues, helps to increase bone mass at the spine.

Fortical® Nasal Spray is taken with calcium and vitamin D supplements recommended by your doctor, to help slow down further bone loss. If you are not getting enough calcium and vitamin D in your daily diet, your doctor may recommend a calcium or vitamin D supplement. The amount of calcium and vitamin D needed each day can vary from person to person. Most people generally require at least 1000 mg of calcium and 400 International Units of vitamin D each day. Vitamin D is necessary for your body to use calcium to build bone material. That is why your doctor may have recommended that you add a vitamin D supplement to your diet. It is important to take all the calcium and vitamin D supplements your doctor directs each day.

Who should not use Fortical® Nasal Spray?

Do not use Fortical® Nasal Spray if you are allergic to the calcitonin salmon protein.

What should I tell my doctor before using Fortical® Nasal Spray?

Tell your doctor about all your health conditions, including if you:

- are pregnant. It is not known if Fortical® Nasal Spray can cause harm to an unborn baby if it is used during pregnancy.
- are breast-feeding. It is not known if Fortical® Nasal Spray passes into your breast milk.

Tell your doctor and pharmacist about all the medicines you take, including prescription and non-prescription medicines, vitamins and herbal supplements.

Know the medicines you take. Keep a list of your medicines and show it to your doctor and pharmacist when you get a new medicine.

How should I use Fortical® Nasal Spray?

- Periodic nasal exams are recommended. Your doctor should do a nasal exam before you start using Fortical® Nasal Spray and if you have any nasal discomfort while using it.
- Use Fortical® Nasal Spray exactly as your doctor prescribes it. See the detailed Patient Instructions for Use at the end of this leaflet.
- Before using a new bottle of Fortical® Nasal Spray for the first time, take it out of the refrigerator and let the medicine warm to room temperature. Using Fortical® Nasal Spray directly from a refrigerator without being warmed to room temperature may cause you to have nasal discomfort.
- Before using a new bottle of Fortical® Nasal Spray for the first time, you will need to prime the pump at least 5 times until a full spray is produced. See the detailed Assembly Instructions and Using Fortical® Nasal Spray sections at the end of this Patient Information Leaflet for directions on how to prime a new bottle of Fortical® Nasal Spray and how to properly use Fortical® Nasal Spray.
- One spray in either nostril will give you the right daily dose of Fortical® Nasal Spray. Change (alternate) between using the right nostril one day and the left nostril the next day. Each bottle of Fortical® Nasal Spray contains enough medicine for 30 days of dosing.
- After priming the pump, do not use Fortical® Nasal Spray for more than 30 doses. Even though the container may not be completely empty, you may not get the correct dose of medicine. Safely throw away the empty bottle of Fortical® Nasal Spray after you have used 30 doses.
- If you miss a dose, or forget to use Fortical® Nasal Spray, use it as soon as you can. If it is almost time for your next dose, wait until then to use the medicine and skip the missed dose. Do not use extra medicine to make up for the missed dose.
- If you use too much Fortical® Nasal Spray, tell your doctor.

What are the possible side effects of Fortical® Nasal Spray?

Serious allergic reactions can happen with Fortical® Nasal Spray. See "Who should not use Fortical® Nasal Spray".

Get emergency medical help right away if you have any of the following symptoms of a serious allergic reaction:

- trouble breathing
- swelling of your face, throat or tongue
- rapid heartbeat
- chest pain
- feel faint or dizzy

The most common side effects of Fortical® Nasal Spray include:

- nasal symptoms including: runny nose, dryness, crusting, sores, infection, redness, irritation, itching, tenderness, nosebleed, discomfort across bridge of nose
- back and joint pain
- headache

Tell your doctor if you have any side effect that bothers you or that does not go away. These are not all the possible side effects of Fortical® Nasal Spray. For more information, ask your doctor or pharmacist.

How should I store Fortical® Nasal Spray?

- Keep new, unopened bottles of Fortical® Nasal Spray in the refrigerator, between 36°F to 46°F (2°C to 8°C).
- Do not freeze.
- Keep the bottle of Fortical® Nasal Spray away from light.
- Allow the Fortical® Nasal Spray to reach room temperature before using it and for the first time.
- Tighten the pump securely to the bottle (see Step 3 and 4 in the Patient Instructions of Use - Assembly Instructions). This will help to ensure a good seal between the pump and the bottle.
- After opening a new bottle of Fortical® Nasal Spray, store at room temperature, 68°F to 77°F (20°C to 25°C).
- Each bottle of Fortical® Nasal Spray contains enough medicine for 30 doses. Throw away the empty bottle of Fortical® Nasal Spray after you have used 30 doses.

Keep Fortical® Nasal Spray and all other medicines out of the reach of children.

What are the ingredients in Fortical® Nasal Spray?

Active Ingredient: Calcitonin-salmon

Inactive Ingredients: Sodium Chloride USP, Citric Acid USP, Phenethyl Alcohol USP, Benzyl Alcohol NF, Polysorbate 80 NF, Hydrochloric Acid NF or Sodium Hydroxide NF and Purified Water USP.

General Information about Fortical® Nasal Spray

This medication was prescribed for you by your doctor for a particular condition. Do not use Fortical® Nasal Spray to treat a condition for which it was not prescribed. Do not give Fortical® Nasal Spray to other people, even if they have the same symptoms you have. It may harm them.

This patient information leaflet summarizes the most important information about Fortical® Nasal Spray. If you would like more information about Fortical® Nasal Spray talk with your doctor. You can ask your doctor or pharmacist for information about Fortical® Nasal Spray that is written for health professionals. For more information, go to www.upsher-smith.com or call 1-800-654-2299.

General Information about Osteoporosis

The amount of estrogen produced by a woman's body is greatly reduced after menopause. Estrogen helps to balance bone growth and keep bones strong. When estrogen is reduced, your body may remove old bone cells faster than it replaces them with new bones cells. Bones can become weak and brittle, and more likely to break (fracture). This condition is known as postmenopausal osteoporosis. Fortical® Nasal Spray may increase bone density, but there is no information to show that it decreases the risk of fracture.

Patient Instructions for Use

Assembly Instructions

Step 1. Opening the Bottle. If your pharmacist attached the pump for you, skip to step 4. Otherwise, set bottle on a flat surface like table or counter top. Hold the bottle firmly while unscrewing cap to avoid spilling any Fortical® Nasal Spray.

Step 2. Unwrapping the Pump. Carefully cut the wrapper with scissors or knife, and tear away from the pump. Be careful not to cut, bend, or touch the feed tube at bottom.

Step 3. Attaching the Pump. Hold the bottle on a flat surface (like a table), and screw the pump onto bottle by gripping the grooves of the pump and twisting clockwise until the pump is tightly sealed to the bottle.

Step 4. Removing Cap. To remove the cap from the pump, twist slightly while pulling up. Save the cap to replace after each use.

Save the lock tab, and push it back on to the pump after each use to avoid accidentally wasting any Fortical® Nasal Spray

Step 5. Removing the Lock Tab. Grasp the lock tab between thumb and forefinger, while holding the bottle on a flat surface. Pull sideways to remove the tab and unlock the pump.

Step 6. Prime New Pump Before First Use.
Before you use a new bottle of Fortical® Nasal Spray for the first time, you will need to prime it. This will ensure you get the right dose of medicine each time you use it. After you attach the pump to the bottle, and the pump and bottle have reached room temperature, you should:

- Hold the bottle upright.
- With your index and middle fingers on each side of the top of the pump, and with your thumb under the bottle, push the pump down.
- Push the pump down at least 5 times, until you see a full spray.
- If the pump is not delivering a full spray during or after priming, contact Upsher-Smith at 1-800-654-2299. Do not place anything into the opening of the pump.

You only need to prime a new bottle. Do NOT re-prime it before each use.

Using Fortical® Nasal Spray...

Step 7. Using Fortical® Nasal Spray

- Change (alternate) between using the right nostril one day and the left nostril the next day.
- Hold your head and the bottle in an upright, vertical position. Put the spray tip into your nostril at the same angle as your nasal passage.

- Press the pump all the way down one time. You do not need to inhale.
- If you do not hold the bottle upright during use, the pump may not be able to give you the right dose of medicine.
- You may not feel the spray because the mist is so fine. Do not waste medication by testing the sprayer. It is all right if some of the spray drips out of your nostril. One spray will give you the correct daily dose of Fortical® Nasal Spray.

Step 8. Replace The Lock Tab After Use. Replace the lock tab to prevent wasting medication by accidently depressing the pump. Simply slide the lock tab on by pushing it sideways against the grooves in the pump.

Step 9. Replace The Cap.

- Hold the top of the pump as shown in diagram 9., and slide the cap back over the tip carefully.
- Do NOT put the pump back in the refrigerator.

Store Fortical® Nasal Spray in an upright position. Tighten the pump securely to the bottle (see Step 3 and 4 in the Patient Instructions for Use). This will help to ensure a good seal between the pump and the bottle.

Cleaning the Pump. Clean the spray tip by gently wiping it with a clean, damp cloth or tissue. Dry the tip with a cloth or tissue before replacing the cap. Do not submerse the tip or bottle in water.

Upsher-Smith Laboratories, Inc.
Minneapolis, MN USA 55447-4709
www.upsher-smith.com

Toll Free 1-800-654-2299

103001-01
Revised 0609
UPSHER-SMITH

PRINCIPAL DISPLAY PANEL - 2200 IU/mL Carton

Fortical®
calcitonin-salmon
(rDNA origin)
Nasal Spray

200 International Units/dose
2200 IU/mL

REFRIGERATE
UNTIL OPENED
at 36-46°F (2-8°C)

FOR INTRANASAL USE ONLY

30 doses
Each carton contains:
1 × 3.7 mL fill bottle and
1 spray applicator Rx only